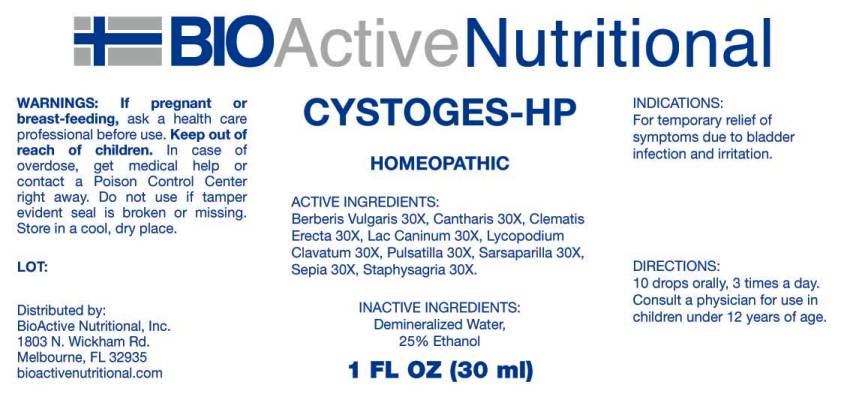 DRUG LABEL: Cystoges
NDC: 43857-0064 | Form: LIQUID
Manufacturer: BioActive Nutritional, Inc.
Category: homeopathic | Type: HUMAN OTC DRUG LABEL
Date: 20231103

ACTIVE INGREDIENTS: LYTTA VESICATORIA 30 [hp_X]/1 mL; BERBERIS VULGARIS ROOT BARK 30 [hp_X]/1 mL; CANIS LUPUS FAMILIARIS MILK 30 [hp_X]/1 mL; CLEMATIS RECTA FLOWERING TOP 30 [hp_X]/1 mL; LYCOPODIUM CLAVATUM SPORE 30 [hp_X]/1 mL; DELPHINIUM STAPHISAGRIA SEED 30 [hp_X]/1 mL; PULSATILLA VULGARIS WHOLE 30 [hp_X]/1 mL; SEPIA OFFICINALIS JUICE 30 [hp_X]/1 mL; SMILAX ORNATA ROOT 30 [hp_X]/1 mL
INACTIVE INGREDIENTS: WATER; ALCOHOL

DRUG FACTS:

ACTIVE INGREDIENTS:

Berberis Vulgaris 30X, Cantharis 30X, Clematis Erecta 30X, Lac Caninum 30X, Lycopodium Clavatum 30X, Pulsatilla 30X, Sarsaparilla 30X, Sepia 30X, Staphysagria 30X.

INDICATIONS:

For temporary relief of symptoms due to bladder infection and irritation.

WARNINGS:

If pregnant or breast-feeding, ask a health care professional before use.

Keep out of reach of children. In case of overdose, get medical help or contact a Poison Control Center right away.

Do not use if tamper evident seal is broken or missing.

Store in cool, dry place.

DIRECTIONS:

10 drops orally, 3 times a day. Consult a physician for use in children under 12 years of age.

INACTIVE INGREDIENTS:

Demineralized Water, 25% Ethanol

KEEP OUT OF REACH OF CHILDREN:

In case of overdose, get medical help or contact a Poison Control Center right away.

INDICATIONS:

For temporary relief of symptoms due to bladder infection and irritation.

QUESTIONS:

Distributed by:
BioActive Nutritional, Inc.
1803 N. Wickham Rd.
Melbourne, FL 32935
bioactivenutritional.com

PACKAGE LABEL DISPLAY:

BIOActive Nutritional

HOMEOPATHIC

1 FL OZ (30 ml)